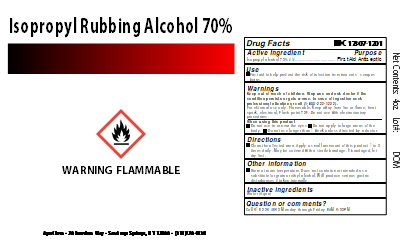 DRUG LABEL: Isopropyl Rubbing Alcohol 70%
NDC: 17307-1201 | Form: SOLUTION
Manufacturer: AgroChem, Inc
Category: otc | Type: HUMAN OTC DRUG LABEL
Date: 20200921

ACTIVE INGREDIENTS: ISOPROPYL ALCOHOL 0.7 mL/1 mL
INACTIVE INGREDIENTS: WATER

Isopropyl Rubbing Alcohol 70%

DESCRIPTION

Isopropyl Rubbing Alcohol 70%

Active Ingredient(s)

Isopropyl alcohol 70% v/v Purpose:First Aid Antiseptic

Purpose

First Aid Antiseptic

Use

First aid to help prevent the risk of infection in: ∙ minor cuts ∙ scrapes ∙ burns.

Warnings

For external use only. Flammable. Keep away from heat or flame, heat spark, electrical, Flash point 72F ∙ do not use with electrocautery procedures.

Do not use

When using this product ∙ do not use in or near the eyes ∙ do not apply to large areas of the body ∙ do not use longer than 1 week unless directed by a doctor

Ask a doctor before use if you have deep or puncture wounds, animal bites or serious burns.

Ask a doctor before use if the condition persists or gets worse

Keep out of reach of children. In case of accidental ingestion seek professional assistance or contact Poison Control Center (1-800-222-1222)

Directions

Clean the affected area. Apply a small amount of this product 1 to 3 times daily May be covered with a sterile bandage.

If bandaged, let dry first..

Other information

Store at room temperature ∙ does not contain nor intended as a substitute for grain or ethyl alcohol ∙ will produce serious gastric disturbances if taken internally.

Inactive ingredients

Water (Aqua)

Package Label - Principal Display Panel

118 mL NDC: 17307-1201-1